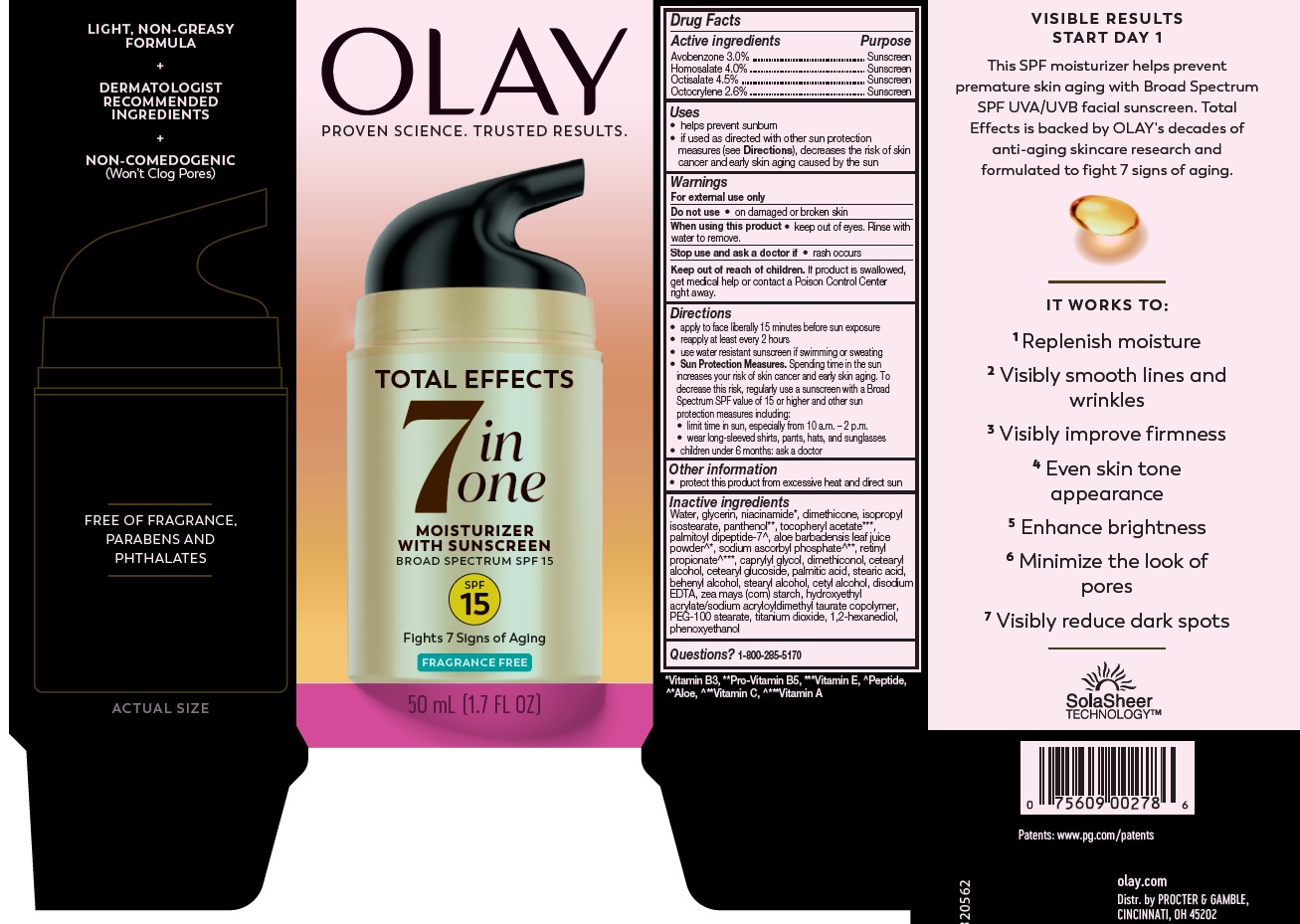 DRUG LABEL: Olay Total Effects Moisturizer with Sunscreen
NDC: 69423-388 | Form: LOTION
Manufacturer: The Procter & Gamble Manufacturing Company
Category: otc | Type: HUMAN OTC DRUG LABEL
Date: 20250819

ACTIVE INGREDIENTS: AVOBENZONE 3 g/100 mL; HOMOSALATE 4 g/100 mL; OCTISALATE 4.5 g/100 mL; OCTOCRYLENE 2.6 g/100 mL
INACTIVE INGREDIENTS: RETINYL PROPIONATE; HYDROXYETHYL ACRYLATE/SODIUM ACRYLOYLDIMETHYL TAURATE COPOLYMER (100000 MPA.S AT 1.5%); PALMITIC ACID; CETEARYL ALCOHOL; WATER; GLYCERIN; NIACINAMIDE; DIMETHICONE; ISOPROPYL ISOSTEARATE; PANTHENOL; .ALPHA.-TOCOPHEROL ACETATE; TITANIUM DIOXIDE; STEARYL ALCOHOL; BEHENYL ALCOHOL; CETYL ALCOHOL; PEG-100 STEARATE; SODIUM ASCORBYL PHOSPHATE; CETEARYL GLUCOSIDE; STEARIC ACID; EDETATE DISODIUM; ZEA MAYS (CORN) STARCH; DIMETHICONOL (50000 CST); ALOE BARBADENSIS LEAF POWDER; PHENOXYETHANOL; PALMITOYL DIPEPTIDE-7; CAPRYLYL GLYCOL; 1,2-HEXANEDIOL

Olay® Total Effects® Moisturizer
Broad Spectrum SPF 15 Fragrance Free

Drug Facts

ACTIVE INGREDIENT

Active ingredients | Purpose
Avobenzone 3.0% | Sunscreen
Homosalate 4.0% | Sunscreen
Octisalate 4.5% | Sunscreen
Octocrylene 2.6% | Sunscreen

Uses

- helps prevent sunburn
- if used as directed with other sun protection measures (see Directions), decreases the risk of skin cancer and early skin aging caused by the sun

Warnings

For external use only

Do not use

- on damaged or broken skin

When using this product

- keep out of eyes. Rinse with water to remove.

Stop use and ask a doctor if

- rash occurs

Keep out of reach of children. If product is swallowed, get medical help or contact a Poison Control Center right away.

Directions

- apply liberally 15 minutes before sun exposure
- reapply at least every 2 hours
- use water resistant sunscreen if swimming or sweating
- Sun Protection Measures. Spending time in the sun increases your risk of skin cancer and early skin aging. To decrease this risk, regularly use a sunscreen with a Broad Spectrum SPF value of 15 or higher and other sun protection measures including:
  - limit time in sun, especially from 10 a.m. - 2 p.m.
  - wear long-sleeved shirts, pants, hats, and sunglasses
- children under 6 months: ask a doctor

Other information

- protect this product from excessive heat and direct sun

Inactive ingredients

Water, glycerin, niacinamide, dimethicone, isopropylisostearate, panthenol, tocopheryl acetate, palmitoyl dipeptide-7, aloe barbadensis leaf juice powder, sodium ascorbyl phosphate, retinyl propionate, caprylyl glycol, dimethiconol, cetearyl alcohol, cetearyl glucoside, palmitic acid, stearic acid, behenyl alcohol, stearyl alcohol, cetyl alcohol, disodium EDTA, zea mays (corn) starch, hydroxyethyl acrylate/sodium acryloyldimethyl taurate copolymer, PEG-100 stearate, titanium dioxide, 1,2-hexanediol, phenoxyethanol

Questions or comments?

Call 1-800-285-5170

Distr. by PROCTER & GAMBLE,
CINCINNATI, OH 45202

PRINCIPAL DISPLAY PANEL - 50 mL Bottle Carton

OLAY

TOTAL EFFECTS

7 IN

ONE

MOISTURIZER WITH sunscreen

BROAD SPECTRUM SPF 15
FRAGRANCE-FREE

50 mL (1.7 FL OZ)